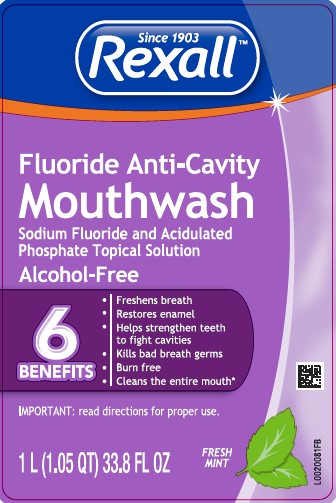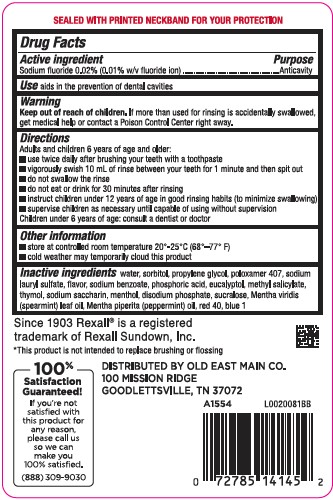 DRUG LABEL: Anticavity
NDC: 55910-971 | Form: RINSE
Manufacturer: Old East Main Co.
Category: otc | Type: HUMAN OTC DRUG LABEL
Date: 20260302

ACTIVE INGREDIENTS: SODIUM FLUORIDE 0.1 mg/1 mL
INACTIVE INGREDIENTS: WATER; SORBITOL; PROPYLENE GLYCOL; POLOXAMER 407; SODIUM LAURYL SULFATE; SODIUM BENZOATE; PHOSPHORIC ACID; EUCALYPTOL; METHYL SALICYLATE; THYMOL; SACCHARIN SODIUM; MENTHOL, UNSPECIFIED FORM; SODIUM PHOSPHATE, DIBASIC, ANHYDROUS; SUCRALOSE; SPEARMINT OIL; PEPPERMINT OIL; FD&C RED NO. 40; FD&C BLUE NO. 1

Rexall 971.001/971AB
Anticavity Fluoride Rinse

TAMPER EVIDENT STATEMENT

Sealed with printed neckband for your protection.

Active Ingredient

Sodium fluoride 0.02% (0.01% w/v fluoride ion)

Purpose

Anticavity

Use

aids in the prevention of dental cavities

Warning

for this product

Keep out of Reach of Children

If more than used for rinsing is accidentally swallowed, get medical help or contact a Poison Control Center right away.

Directions

Adults and children 6 years of age and older:

- use twice daily after brushing your teeth with a toothpaste
- vigorously swish 10 mL of rinse between your teeth for 1 miute and then spit out.
- do not swallow the rinse
- do not eat or drink for 30 minutes after rinsing
- instruct children under 12 years of age in good rinsing habits (to minimize swallowing)
- supervise children as necessary until capable of using without supervision

Children under 6 years of age: consult a dentist or doctor

Other information

- store at room temperature 20⁰ - 25⁰ C (68⁰ - 77⁰ F)
- cold weather may temporarily cloud this product

Inactive ingredients

water, sorbitol, propylene glycol, poloxamer 407, sodium lauryl sulfate, flavor, sodium benzoate, phosphoric acid, eucalyptol, methyl salicylate, thymol, sodium saccharin, menthol, disodium phosphate, sucralose, Mentha viridis (spearmint) leaf oil, Mentha piperita (peppermint) oil, red 40, blue 1

Disclaimer

Since 1903 Rexall®is a registered trademark of Rexall Sundown, Inc.

*This product is not intended to replace brushing or flossing

Adverse Reaction

100% Satisfaction Guaranteed

If you're not satisfied with this product for any reason, please call us so we can make you 100% satisfied.

(888)309-9030

DISTRIBUTED BY OLD EAST MAIN CO.

100 MISSION RIDGE

GOODLETTSVILLE, TN 37072

principal panel display

Since 1903

Rexall™

Fluoride Anti-Cavity

Mouthwash

Sodium Fluoride and Acidulated

Phosphate Topical Solution

Alcohol-Free

6 BENEFITS

- Freshens breath
- Restores enamel
- Helps strengthen teeth to fight cavities
- Kills bad breath germs
- Burn free
- Cleans the entire mouth*

IMPORTANT: read directions for proper use.

FRESH MINT

1 L (1.05 QT) 33.8 FL OZ